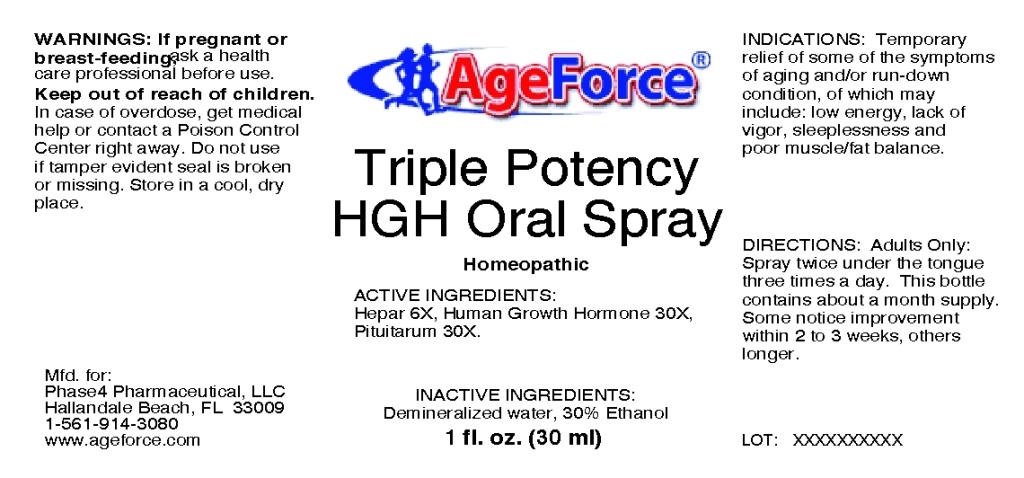 DRUG LABEL: Triple Potency HGH
NDC: 57520-0648 | Form: SPRAY
Manufacturer: Apotheca Company
Category: homeopathic | Type: HUMAN OTC DRUG LABEL
Date: 20110329

ACTIVE INGREDIENTS: SOMATROPIN 30 [hp_X]/1 mL; PORK LIVER 6 [hp_X]/1 mL; SUS SCROFA PITUITARY GLAND 30 [hp_X]/1 mL
INACTIVE INGREDIENTS: WATER; ALCOHOL

Triple Potency HGH Oral Spray

ACTIVE INGREDIENT

ACTIVE INGREDIENTS: Hepar 6X, Human growth hormone 30X, Pituitarum 30X.

PURPOSE

INDICATIONS: Temporary relief of some of the symptoms of aging and/or run-down condition, of which may include: low energy, lack of vigor, sleeplessness and poor muscle/fat balance.

WARNINGS

WARNINGS: If pregnant or breast-feeding, ask a health care professional before use.

Keep out of reach of children. In case of overdose, get medical help or contact a Poison Control Center right away.

Do not use if tamper evident seal is broken or missing. Store in a cool, dry place.

DOSAGE AND ADMINISTRATION

DIRECTIONS: Adults Only: Spray twice under the tongue three times a day. This bottle contains about a month supply. Some notice improvement within 2 to 3 weeks, others longer.

INACTIVE INGREDIENTS: Demineralized water, 30% Ethanol.

KEEP OUT OF REACH OF CHILDREN. In case of overdose, get medical help or contact a Poison Control Center right away.

INDICATIONS AND USAGE

INDICATIONS: Temporary relief of some of the symptoms of aging and/or run-down condition, of which may include: low energy, lack of vigor, sleeplessness and poor muscle/fat balance.

QUESTIONS

Mfd. for:

Phase4 Pharmaceutical, LLC

Hallandale Beach, FL 33009

1-561-914-3080

www.ageforce.com

PACKAGE LABEL

AgeForce

Triple Potency HGH Oral Spray

Homeopathic

1 fl. oz. (30 ml)